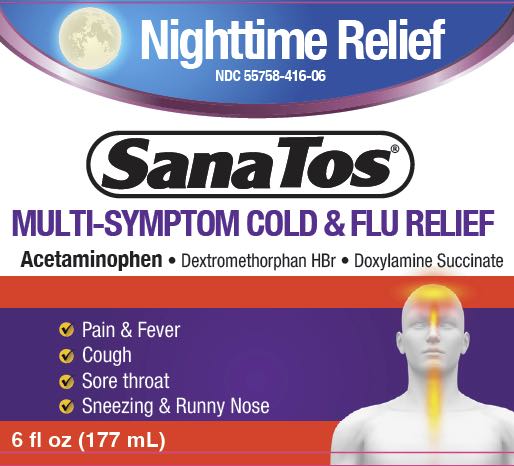 DRUG LABEL: Sanatos
NDC: 55758-416 | Form: LIQUID
Manufacturer: Pharmadel LLC
Category: otc | Type: HUMAN OTC DRUG LABEL
Date: 20231122

ACTIVE INGREDIENTS: ACETAMINOPHEN 650 mg/30 mL; DOXYLAMINE SUCCINATE 12.5 mg/30 mL; DEXTROMETHORPHAN HYDROBROMIDE 30 mg/30 mL
INACTIVE INGREDIENTS: ANHYDROUS CITRIC ACID; FD&C GREEN NO. 3; FD&C YELLOW NO. 6; SUCRALOSE; SODIUM BENZOATE; SODIUM CITRATE; SORBITOL SOLUTION; WATER; D&C YELLOW NO. 10; GLYCERIN; PROPYLENE GLYCOL; XANTHAN GUM

Sanatos Nighttime MS 6 (PLE)

Active ingredients & Purposes

PURPOSE

Active ingredients; (in each 30 mL) | Purposes
Acetaminophen 650 mg | Pain reliever/ fever reducer
Dextromethorphan HBr 30 mg | Cough suppressant
Doxylamine succinate 12.5 mg | Antihistamine

Uses

Temporarily relieves common cold/flu symptoms associated with

- minor aches and pains
- headache
- sore throat
- runny nose
- cough due to minor throat and bronchial irritation
- sneezing
- temoprarily reduces fever

Warnings

Liver warning: This product contains acetaminophen. Severe liver damage may occur if you take:

- adults take more than 4 doses in 24 hours, which is the maxium daily amount
- child takes more than 3 doses in 24 hours
- taken with other drugs containing acetaminophen
- adult has 3 or more alcoholic drinks everyday while using this product

Sore throat warning: If sore throat is severe, persists for more than 2 days, is accompanied or followed by fever, headache, rash, nausea, or vomiting, consult a doctor promptly.

Do not use

- with any other drug containing acetaminophen (prescription or nonprescription). If you are not sure whether a drug contains acetaminophen, ask a doctor or pharmacist.
- if you are now taking a prescription monoamine oxidase inhibitor (MAOI) (certain drugs for depression, psychiatric or emotional conditions, or Parkinson's disease), or for 2 weeks after stopping the MAOI drug. If you do not know if your prescription drug contains an MAOI, ask a doctor or pharmacist before taking this product.

Ask a doctor before use if user

- has a sodium-restricted diet
- has liver disease
- has glaucoma
- has cough that occurs with too much phlegm (mucus)
- has a breathing problem or chronic cough that lasts or as occurs with smoking, asthma, chronic bronchitis, or emphysema
- has trouble urinating due to enlarged prostate gland
- is a child with pain of arthritis

Ask a doctor or pharmacist before use if user is

- taking the blood thinning drug warfarin
- taking sedatives or tranquilizers

When using this product

- excitability may occur, especially in children
- may cause marked drowsiness; alcohol, sedatives, and tranquilizers may increase the drowsiness effect
- avoid alcoholic beverages
- use caution when driving a motor vehicle or operating machinery

Stop use and ask a doctor if

- pain or cough gets worse or lasts more than 5 days (children) or 7 days (adults)
- fever gets worse or lasts more than 3 days
- redness or swelling is present
- any new symptoms occur
- cough comes back, or occurs with rash or headache that lasts.

These could be signs of a serious condition.

If pregnant or breast-feeding,

ask a health professional before use.

Keep out of reach of children.

In case of overdose, get medical help or contact a Poison Control Center right away. Prompt medical attention is critical for adults as well as for children even if you do not notice any signs or symptoms.

Directions

- use only dosing cup provided
- shake well before use
- if you are taking other cold/flu products, read complete labeling

adults & children 12 years & over | 30 mL every 4 hours, do not exceed (child) 3 doses and (adult) 4 doses in 24 hours
children under 12 years | ask a doctor

Other informaiton

- each 30 mL contains: sodium 10 mg
- store between 68-77°F (20-25°C)

Inactive ingredients

citric acid, D&C yellow#10, FD&C Green# 3, FD&C yellow# 6, flavor, glycerin, polythylene glycol, propylene glycol, purified water, saccharin sodium, sodium benzoate, sodium citrate, sucrose

Questions?

+1-866-359-3478 (M-F) 9AM – 5PM EST or www.pharmadel.com

Distributed by:

Pharmadel

New Castle, DE 19720

www.pharmadel.com

Facebook/PHARMADELUSA